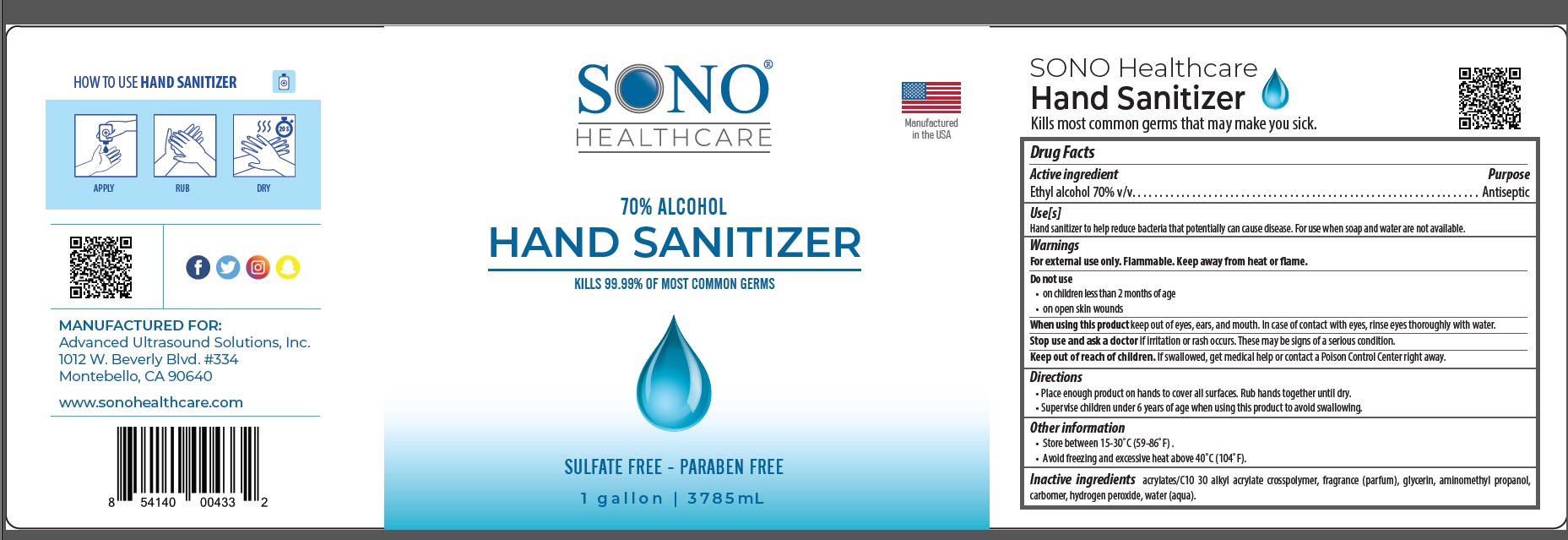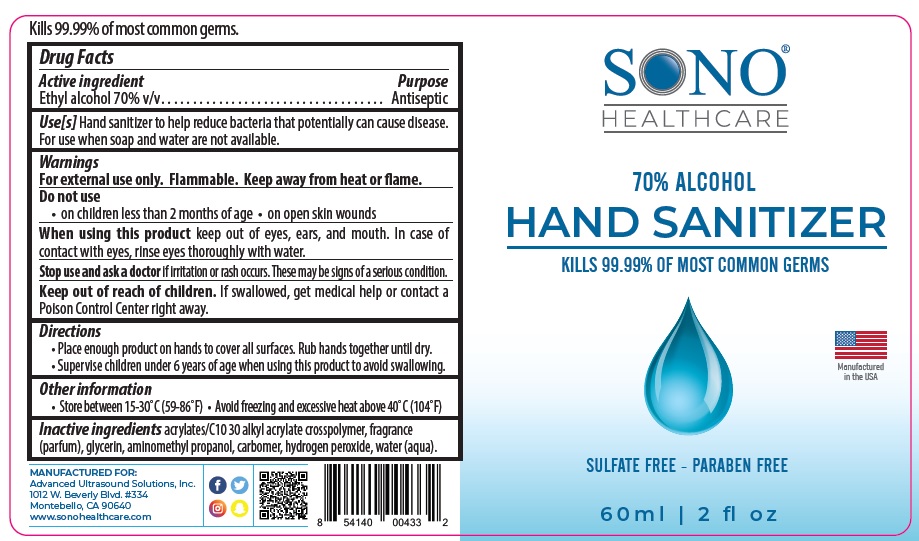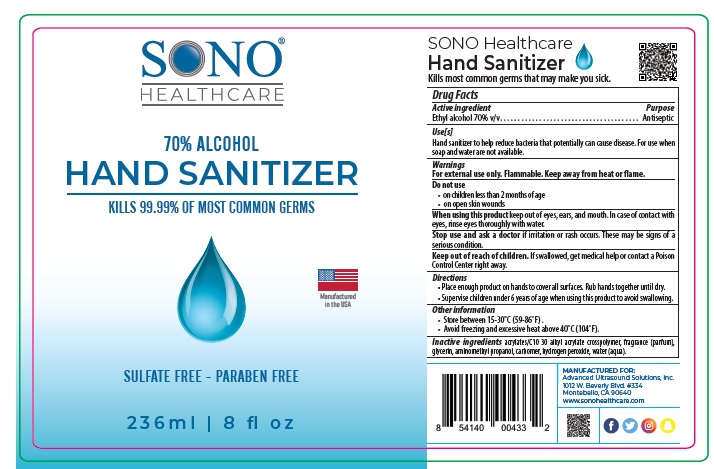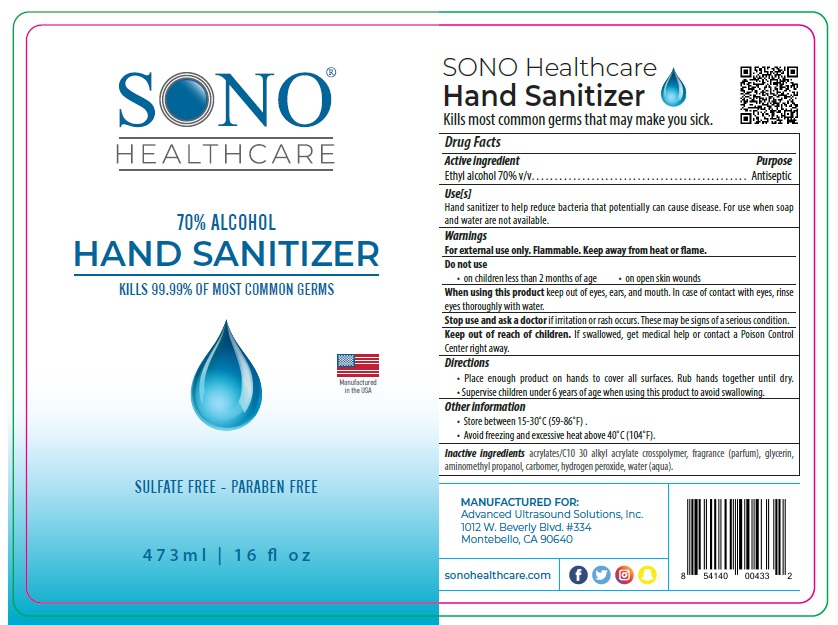 DRUG LABEL: SONO
NDC: 77677-002 | Form: SOLUTION
Manufacturer: Advanced Ultrasound Solutions Inc.
Category: otc | Type: HUMAN OTC DRUG LABEL
Date: 20200909

ACTIVE INGREDIENTS: ALCOHOL 70 mL/100 mL
INACTIVE INGREDIENTS: CARBOMER INTERPOLYMER TYPE A (ALLYL SUCROSE CROSSLINKED); GLYCERIN; AMINOMETHYLPROPANOL; CARBOMER HOMOPOLYMER, UNSPECIFIED TYPE; HYDROGEN PEROXIDE; WATER

Drug Facts

Active Ingredient

Ethyl Alcohol 70%v/v

Purpose

Antiseptic

Uses

Hand sanitizer to help reduce bacteria that potentially can cause disease. For use when soap and water are not available.

Warnings

For external use only. Flammable. Keep away from heat or flame

Do not use

- on children less than 2 months of age
- on open skin wound

When using this product

keep out of reach of eyes, ears, and mouth. In case of contact with eyes, rinse eyes thoroughly with water.

Stop use and ask a doctor

if irritation or rash occurs. These may be signs of a serious condition.

Keep out of reach of children

If swallowed, get medical help or contact a Poison Control Center right away.

Directions

- Place enough product on hands to cover all surfaces. Rub hands together until dry.
- Supervise children under 6 years of age when using this product to avoid swallowing.

Other information

- Store between 15-30°C (59-86°F) .
- Avoid freezing and excessive heat above 40°C (104°F).

Inactive ingredients

acrylates/C10 30 alkyl acrylate crosspolymer, fragrance (parfum), glycerin, aminomethyl propanol, carbomer, hydrogen peroxide, water (aqua).

Principal Display Panel

NDC: 77677-002-02, 77677-002-08, 77677-002-16, 77677-002-01

SONO® HEALTHCARE

MADE IN USA

70% ALCOHOL

HAND SANITIZER

KILLS 99.99% OF MOST COMMON GERMS

SULFATE FREE - PARABEN FREE

e 60 ml | 2 fl oz

e 236 ml | 8 fl oz

e 472 ml | 16 fl oz

e 3785 ml | 1 gallon